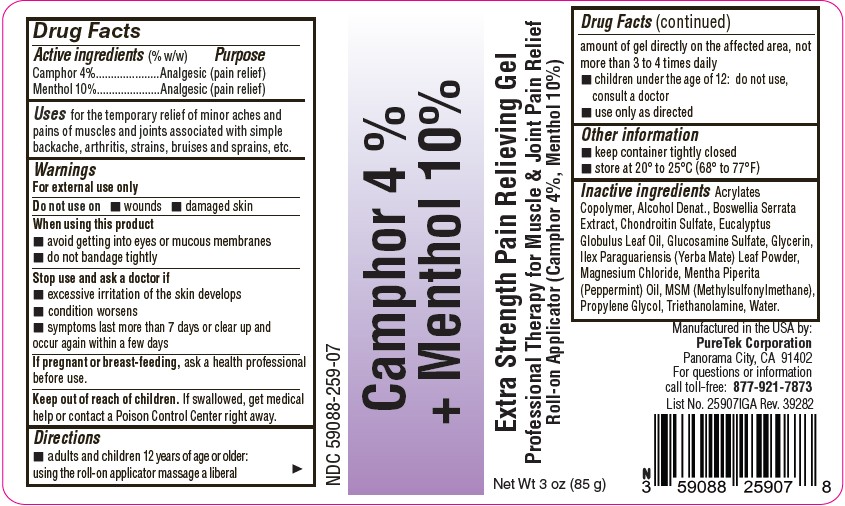 DRUG LABEL: Camphor 4% Plus Menthol 10%
NDC: 59088-259 | Form: GEL
Manufacturer: PureTek Corporation
Category: otc | Type: HUMAN OTC DRUG LABEL
Date: 20250820

ACTIVE INGREDIENTS: MENTHOL 100 mg/1 g; CAMPHOR (SYNTHETIC) 40 mg/1 g
INACTIVE INGREDIENTS: ALCOHOL; ILEX PARAGUARIENSIS LEAF; INDIAN FRANKINCENSE; CHONDROITIN SULFATE (BOVINE); MAGNESIUM CHLORIDE; MENTHA PIPERITA (PEPPERMINT) OIL; PROPYLENE GLYCOL; WATER; GLUCOSAMINE SULFATE; GLYCERIN; EUCALYPTUS GLOBULUS LEAF OIL; DIMETHYL SULFONE; TRIETHANOLAMINE; METHACRYLIC ACID - ETHYL ACRYLATE COPOLYMER (4500 MPA.S)

59088-259-07 Camphor 4% + Menthol 10%

Active Ingredients

Camphor 4%

Menthol 10%

Purpose

Analgesic (pain relief)

Uses

for the temporary relief of minor aches and pains of muscles and joints associated with simple backache, arthritis, strains, bruises and sprains, etc.

Warnings

For external use only

Do not use on

- wounds
- damaged skin

When using this product

- avoid getting into eyes or mucous membranes
- do not bandage tightly

Stop use and ask a doctor if

- excessive irritation of the skin develops
- condition worsens
- symptoms last more than 7 days or clear up and occur again within a few days

If pregnant or breast-feeding

ask a health professional before use.

Keep out of reach of children

If swallowed, get medical help or contact a Poison Control Center right away.

Directions

- adults and children 12 years of age or older: using the roll-on applicator massage a liberal amount of gel directly on the affected area, not more than 3 to 4 times daily.
- children under the age of 12: do not use, consult a doctor
- use only as directed

Other information

- keep container tightly closed
- store at 20° to 25°C (68° to 77°F)

Inactive ingredients

Acrylates Copolymer, Alcohol Denat., Boswellia Serrata Extract, Chondroitin Sulfate, Eucalyptus Globulus Leaf Oil, Glucosamine Sulfate, Glycerin, Ilex Paraguariensis (Yerba Mate) Leaf Powder, Magnesium Chloride, Mentha Piperita (Peppermint) Oil, MSM (Methylsulfonylmethane), Propylene Glycol, Triethanolamine, Water.

Camphor 4 % + Menthol 10%

Manufactured by:

PureTek Corporation
Panorama City, CA 91402
For questions or information
call toll-free: 877-921-7873